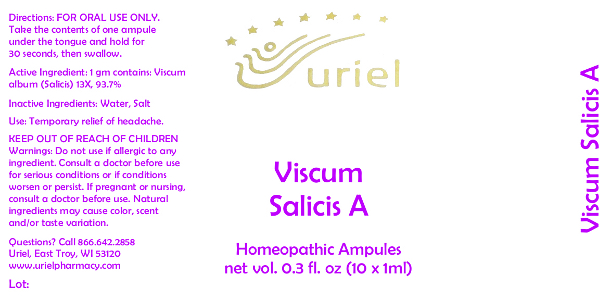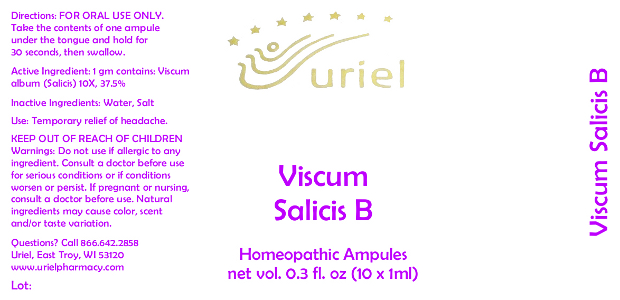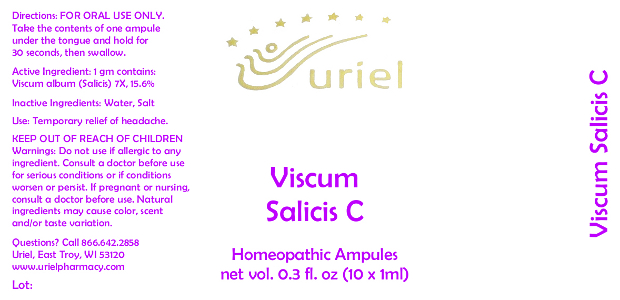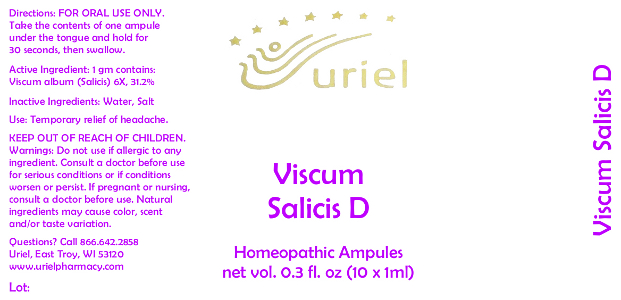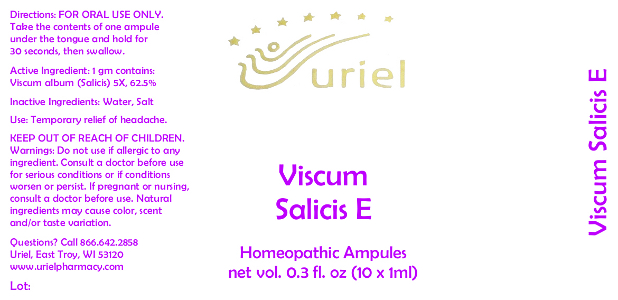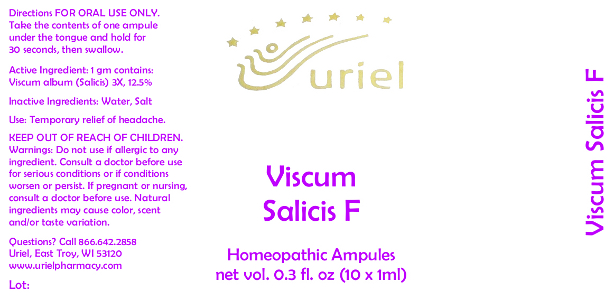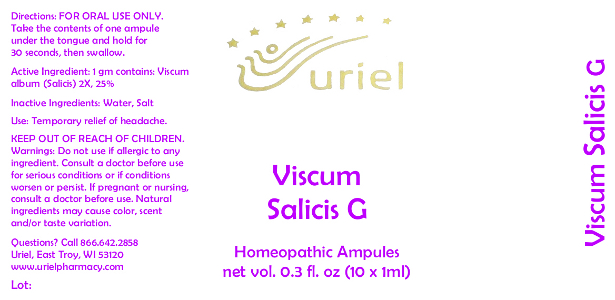 DRUG LABEL: Viscum Salicis
NDC: 48951-1007 | Form: LIQUID
Manufacturer: Uriel Pharmacy Inc
Category: homeopathic | Type: HUMAN OTC DRUG LABEL
Date: 20130130

ACTIVE INGREDIENTS: VISCUM ALBUM FRUITING TOP 2 [hp_X]/1 mL
INACTIVE INGREDIENTS: Water; Sodium Chloride

Viscum Salicis Homeopathic Ampules

DOSAGE AND ADMINISTRATION

Directions: FOR ORAL USE ONLY. Take the contents of one ampule under the tongue and hold for 30 seconds, then swallow.

Active Ingredient: Viscum album (Salicis) | 1 gm contains:
A | 13X 93.7%
B | 10X 37.5%
C | 7X 15.6%
D | 6X 31.2%
E | 5X 62.5%
F | 3X 12.5%
G | 2X 25%

Inactive Ingredients: Water, Salt

INDICATIONS AND USAGE

Use: Temporary relief of headache.

KEEP OUT OF REACH OF CHILDREN.

WARNINGS

Warnings: Do not use if allergic to any ingredient. Consult a doctor before use for serious conditions or if conditions worsen or persist.

PREGNANCY OR BREAST FEEDING

If you are pregnant or nursing, consult a doctor before use.

Natural ingredients may cause color, scent and/or taste variation.

Questions? Call 866 642-2858

Uriel, East Troy, WI 53120

www.urielpharmacy.com